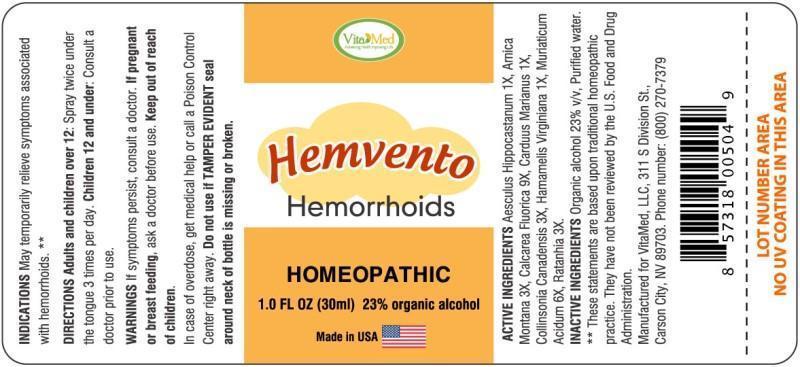 DRUG LABEL: Hemvento
NDC: 64249-0002 | Form: SPRAY
Manufacturer: VitaMed, LLC
Category: homeopathic | Type: HUMAN OTC DRUG LABEL
Date: 20140818

ACTIVE INGREDIENTS: HORSE CHESTNUT 1 [hp_X]/1 mL; ARNICA MONTANA 3 [hp_X]/1 mL; CALCIUM FLUORIDE 9 [hp_X]/1 mL; MILK THISTLE 1 [hp_X]/1 mL; COLLINSONIA CANADENSIS ROOT 3 [hp_X]/1 mL; HAMAMELIS VIRGINIANA ROOT BARK/STEM BARK 1 [hp_X]/1 mL; HYDROCHLORIC ACID 6 [hp_X]/1 mL; KRAMERIA LAPPACEA ROOT 3 [hp_X]/1 mL
INACTIVE INGREDIENTS: WATER; ALCOHOL

DRUG FACTS

ACTIVE INGREDIENTS:

Aesculus Hippocastanum 1X, Arnica Montana 3X, Calcarea Fluorica 9X, Carduus Marianus 1X, Collinsonia Canadensis 3X, Hamamelis Virginiana 1X, Muriaticum Acidum 6X, Ratanhia 3X

INDICATIONS:

May temporarily relieve symptoms associated with hemorrhoids. **

**These statement are based upon traditional homeopathic practice. They have not been reviewed by the U.S. Food and Drug Administration.

WARNINGS:

If symptoms persist, consult a doctor.

If pregnant or breast-feeding, ask a doctor before use.

Keep out of reach of children. In case of overdose, get medical help or call a Poison Control Center right away.

Do not use if TAMPER EVIDENT seal around neck of bottle is missing or broken.

Keep out of reach of children. In case of overdose, get medical help or call a Poison Control Center right away.

DIRECTIONS:

Adults and children over 12: Spray twice under the tongue 3 times per day. Children 12 and under: Consult a doctor prior to use.

INDICATIONS:

May temporarily relieve symptoms associated with hemorrhoids. **

**These statement are based upon traditional homeopathic practice. They have not been reviewed by the U.S. Food and Drug Administration.

INACTIVE INGREDIENTS:

Organic alcohol 23% v/v, Purified water.

QUESTIONS:

Manufactured for VitaMed, LLC 311 S Division St.,

Carson City, NV 89703. Phone number: (800) 270-7379

PACKAGE LABEL DISPLAY

Vita Med

Hemvento

Hemorrhoids

HOMEOPATHIC

1.0 FL OZ (30 ml)